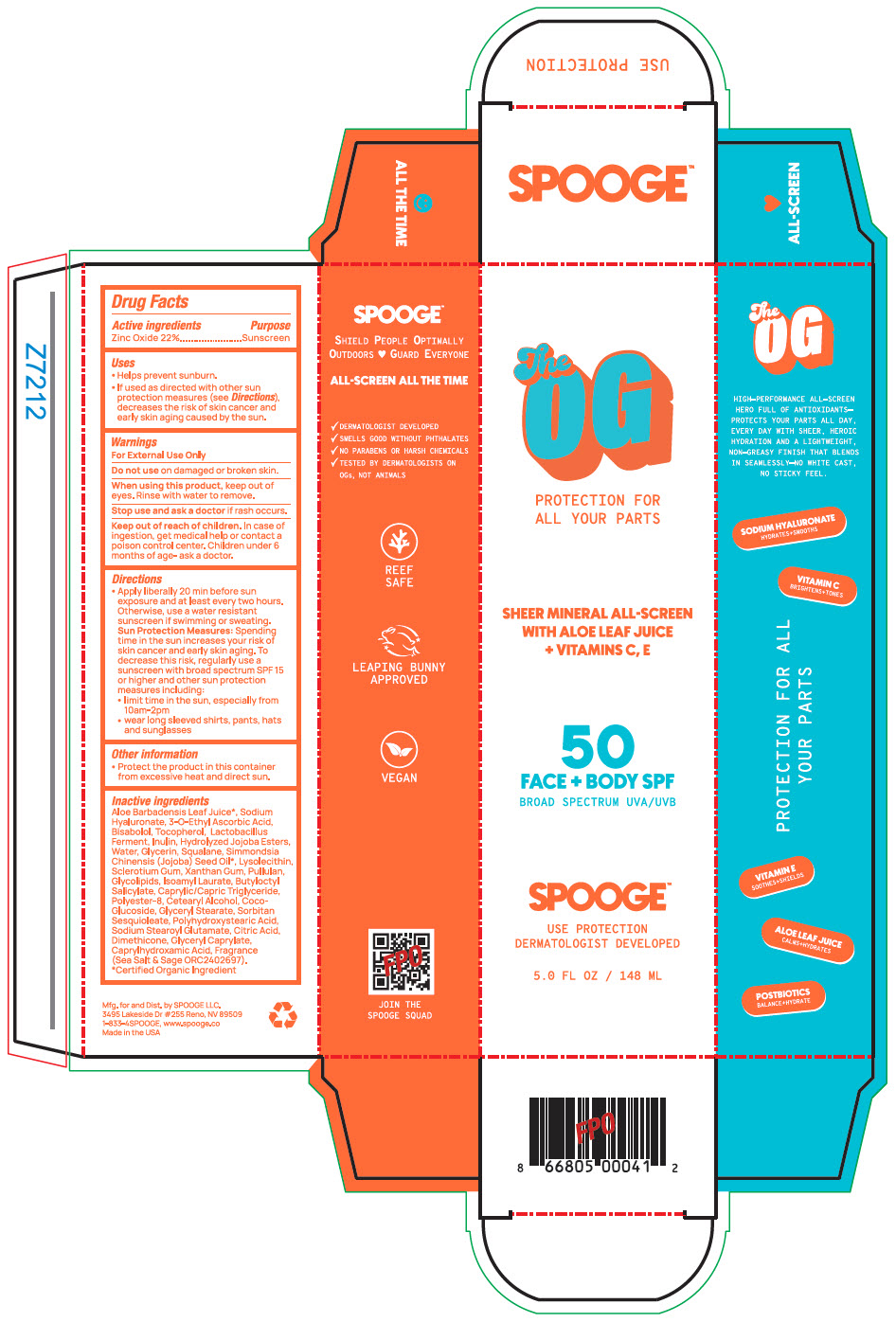 DRUG LABEL: TheOG
NDC: 85385-468 | Form: LOTION
Manufacturer: Spooge
Category: otc | Type: HUMAN OTC DRUG LABEL
Date: 20250626

ACTIVE INGREDIENTS: ZINC OXIDE 22 g/100 mL
INACTIVE INGREDIENTS: ALOE VERA LEAF JUICE; HYALURONATE SODIUM; 3-O-ETHYL ASCORBIC ACID; LEVOMENOL; TOCOPHEROL; HYDROLYZED JOJOBA ESTERS (ACID FORM); WATER; GLYCERIN; SQUALANE; JOJOBA OIL; BETASIZOFIRAN; XANTHAN GUM; PULLULAN; ISOAMYL LAURATE; BUTYLOCTYL SALICYLATE; MEDIUM-CHAIN TRIGLYCERIDES; CETOSTEARYL ALCOHOL; COCO-GLUCOSIDE; GLYCERYL MONOSTEARATE; SORBITAN SESQUIOLEATE; SODIUM STEAROYL GLUTAMATE; CITRIC ACID MONOHYDRATE; DIMETHICONE, UNSPECIFIED; GLYCERYL MONOCAPRYLATE; CAPRYLHYDROXAMIC ACID

TheOG

Drug Facts

Active ingredients

Zinc Oxide 22%

Purpose

Sunscreen

Uses

- Helps prevent sunburn.
- If used as directed with other sun protection measures (see Directions), decreases the risk of skin cancer and early skin aging caused by the sun.

Warnings

For External Use Only

Do not use on damaged or broken skin.

When using this product, keep out of eyes. Rinse with water to remove.

Stop use and ask a doctor if rash occurs.

Keep out of reach of children. In case of ingestion, get medical help or contact a poison control center. Children under 6 months of age- ask a doctor.

Directions

- Apply liberally 20 min before sun exposure and at least every two hours. Otherwise, use a water resistant sunscreen if swimming or sweating.
  Sun Protection Measures: Spending time in the sun increases your risk of skin cancer and early skin aging. To decrease this risk, regularly use a sunscreen with broad spectrum SPF 15 or higher and other sun protection measures including:
  - limit time in the sun, especially from 10am-2pm
  - wear long sleeved shirts, pants, hats and sunglasses

Other information

- Protect the product in this container from excessive heat and direct sun.

Inactive ingredients

Aloe Barbadensis Leaf Juice [certified Organic Ingredient] , Sodium Hyaluronate, 3-O-Ethyl Ascorbic Acid, Bisabolol, Tocopherol, Lactobacillus Ferment, Inulin, Hydrolyzed Jojoba Esters, Water, Glycerin, Squalane, Simmondsia Chinensis (Jojoba) Seed Oil, Lysolecithin, Sclerotium Gum, Xanthan Gum, Pullulan, Glycolipids, Isoamyl Laurate, Butyloctyl Salicylate, Caprylic/Capric Triglyceride, Polyester-a, Cetearyl Alcohol, Coco-Glucoside, Glyceryl Stearate, Sorbitan Sesquioleate, Polyhydroxystearic Acid, Sodium Stearoyl Glutamate, Citric Acid, Dimethicone, Glyceryl Caprylate, Caprylhydroxamic Acid, Fragrance (Sea Salt & Sage ORC2402697).

Dist. by SPOOGE LLC.
3495 Lakeside Dr #255 Reno, NV 89509

PRINCIPAL DISPLAY PANEL - 148 mL Tube Box

The
OG

PROTECTION FOR
ALL YOUR PARTS

SHEER MINERAL ALL-SCREEN
WITH ALOE LEAF JUICE
+ VITAMINS C, E

50
FACE+ BODY SPF
BROAD SPECTRUM UVA/UVB

SPOOGE™

USE PROTECTION
DERMATOLOGIST DEVELOPED

5.0 FL OZ/ 148 ML